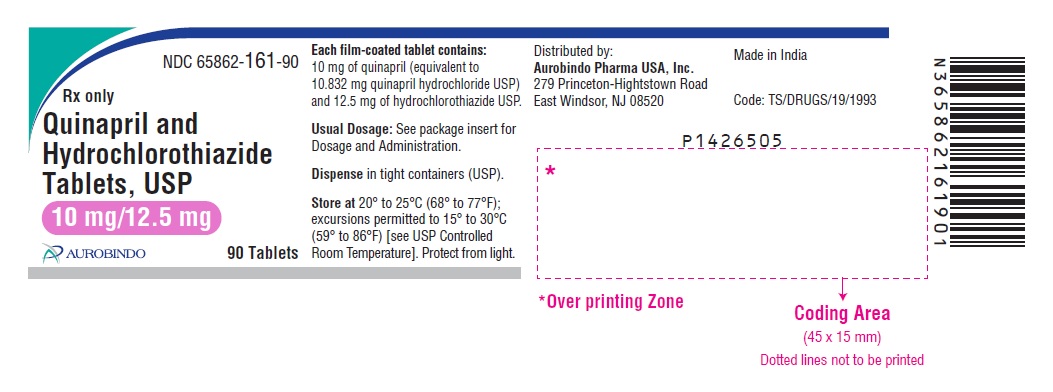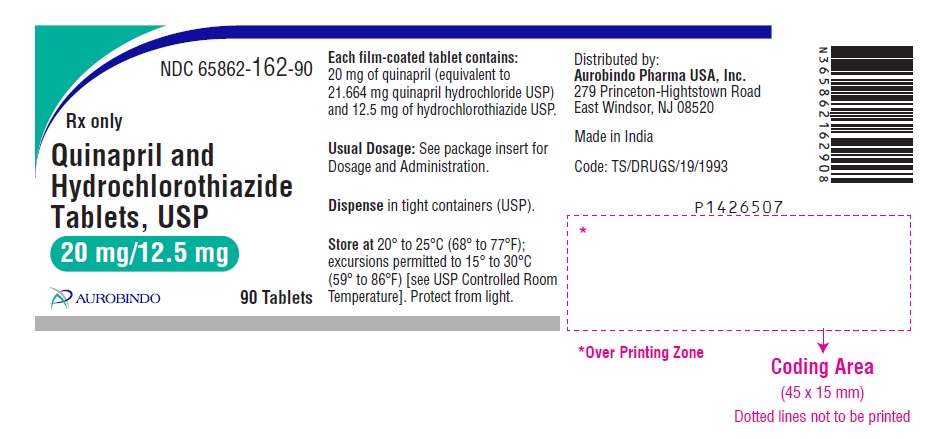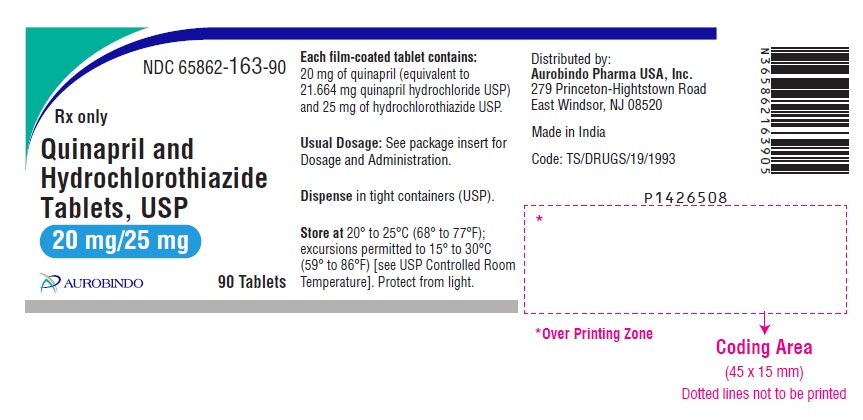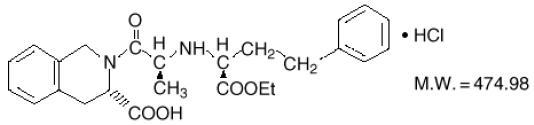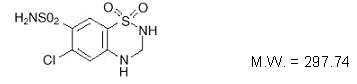 DRUG LABEL: QUINAPRIL HYDROCHLORIDE/HYDROCHLOROTHIAZIDE
NDC: 65862-161 | Form: TABLET, FILM COATED
Manufacturer: Aurobindo Pharma Limited
Category: prescription | Type: Human Prescription Drug Label
Date: 20240428

ACTIVE INGREDIENTS: QUINAPRIL HYDROCHLORIDE 10 mg/1 1; HYDROCHLOROTHIAZIDE 12.5 mg/1 1
INACTIVE INGREDIENTS: LACTOSE MONOHYDRATE; MAGNESIUM CARBONATE; CROSPOVIDONE (120 .MU.M); POVIDONE K30; MAGNESIUM STEARATE; HYPROMELLOSE 2910 (3 MPA.S); HYPROMELLOSE 2910 (50 MPA.S); HYDROXYPROPYL CELLULOSE (1600000 WAMW); POLYETHYLENE GLYCOL 400; TITANIUM DIOXIDE; FERRIC OXIDE RED; FERRIC OXIDE YELLOW

Quinapril and Hydrochlorothiazide Tablets, USP
Rx only

WARNING: FETAL TOXICITY

- When pregnancy is detected, discontinue quinapril and hydrochlorothiazide as soon as possible.
- Drugs that act directly on the renin-angiotensin system can cause injury and death to the developing fetus. See WARNINGS: Fetal Toxicity

DESCRIPTION

Quinapril and hydrochlorothiazide tablets, USP are fixed-combination tablet that combines an angiotensin-converting enzyme (ACE) inhibitor, quinapril hydrochloride, and a thiazide diuretic, hydrochlorothiazide.
Quinapril hydrochloride is chemically described as [3S-[2[R*(R*)], 3R*]]-2-[2-[[1-(ethoxycarbonyl)-3-phenylpropyl]amino]-1-oxopropyl]-1,2,3,4-tetrahydro-3-isoquinolinecarboxylic acid, monohydrochloride. Its molecular formula is C25H30N2O5. HCl and its structural formula is:

Quinapril hydrochloride USP is a white to off-white amorphous powder that is freely soluble in aqueous solvents.
Hydrochlorothiazide is chemically described as: 6-Chloro-3,4-dihydro-2H-1,2,4-benzothiadiazine-7-sulfonamide 1,1-dioxide. Its molecular formula is C7H8ClN3O4S2 and its structural formula is:

Hydrochlorothiazide USP is a white to off-white, crystalline powder which is slightly soluble in water but freely soluble in sodium hydroxide solution.
Quinapril and hydrochlorothiazide tablets, USP are available for oral use as fixed combination tablets in three strengths of quinapril with hydrochlorothiazide: 10 mg (equivalent to 10.832 mg quinapril hydrochloride USP) with 12.5 mg (quinapril and hydrochlorothiazide 10/12.5), 20 mg (equivalent to 21.664 mg quinapril hydrochloride USP) with 12.5 mg (quinapril and hydrochlorothiazide 20/12.5), and 20 mg (equivalent to 21.664 mg quinapril hydrochloride USP) with 25 mg (quinapril and hydrochlorothiazide 20/25). The strength of the quinapril hydrochloride component is in terms of quinapril. Inactive ingredients: lactose monohydrate, magnesium carbonate, crospovidone, povidone, magnesium stearate, hypromellose, hydroxypropyl cellulose, polyethylene glycol 400, titanium dioxide, iron oxide red and iron oxide yellow.

CLINICAL PHARMACOLOGY

Mechanism of Action
The principal metabolite of quinapril, quinaprilat, is an inhibitor of ACE activity in human subjects and animals. ACE is peptidyl dipeptidase that catalyzes the conversion of angiotensin I to the vasoconstrictor, angiotensin II. The effect of quinapril in hypertension appears to result primarily from the inhibition of circulating and tissue ACE activity, thereby reducing angiotensin II formation. Quinapril inhibits the elevation in blood pressure caused by intravenously administered angiotensin I, but has no effect on the pressor response to angiotensin II, norepinephrine, or epinephrine. Angiotensin II also stimulates the secretion of aldosterone from the adrenal cortex, thereby facilitating renal sodium and fluid reabsorption. Reduced aldosterone secretion by quinapril may result in a small increase in serum potassium. In controlled hypertension trials, treatment with quinapril alone resulted in mean increases in potassium of 0.07 mmol/L (see PRECAUTIONS). Removal of angiotensin II negative feedback on renin secretion leads to increased plasma renin activity (PRA).
While the principal mechanism of antihypertensive effect is thought to be through the renin-angiotensin-aldosterone system, quinapril exerts antihypertensive actions even in patients with low renin hypertension. Quinapril was an effective antihypertensive in all races studied, although it was somewhat less effective in blacks (usually a predominantly low renin group) than in non-blacks. ACE is identical to kininase II, an enzyme that degrades bradykinin, a potent peptide vasodilator; whether increased levels of bradykinin play a role in the therapeutic effect of quinapril remains to be elucidated.
Hydrochlorothiazide is a thiazide diuretic. Thiazides affect the renal tubular mechanisms of electrolyte reabsorption, directly increasing excretion of sodium and chloride in approximately equivalent amounts. Indirectly, the diuretic action of hydrochlorothiazide reduces plasma volume, with consequent increases in plasma renin activity, increases in aldosterone secretion, increases in urinary potassium loss, and decreases in serum potassium. The renin-aldolsterone link is mediated by angiotensin, so coadministration of an ACE inhibitor tends to reverse the potassium loss associated with these diuretics.
The mechanism of the antihypertensive effect of thiazides is unknown.
Pharmacokinetics and Metabolism
The rate and extent of absorption of quinapril and hydrochlorothiazide from quinapril and hydrochlorothiazide tablets are not different, respectively, from the rate and extent of absorption of quinapril and hydrochlorothiazide from immediate-release monotherapy formulations, either administered concurrently or separately. Following oral administration of quinapril monotherapy tablets, peak plasma quinapril concentrations are observed within 1 hour. Based on recovery of quinapril and its metabolites in urine, the extent of absorption is at least 60%. The absorption of hydrochlorothiazide is somewhat slower (1 to 2.5 hours) and more complete (50% to 80%).
The rate of quinapril absorption was reduced by 14% when quinapril and hydrochlorothiazide tablets were administered with a high-fat meal as compared to fasting, while the extent of absorption was not affected. The rate of hydrochlorothiazide absorption was reduced by 12% when quinapril and hydrochlorothiazide tablets were administered with a high-fat meal, while the extent of absorption was not significantly affected. Therefore, quinapril and hydrochlorothiazide may be administered without regard to food.
Following absorption, quinapril is deesterified to its major active metabolite, quinaprilat (about 38% of oral dose), and to other minor inactive metabolites. Following multiple oral dosing of quinapril, there is an effective accumulation half-life of quinaprilat of approximately 3 hours, and peak plasma quinaprilat concentrations are observed approximately 2 hours postdose. Approximately 97% of either quinapril or quinaprilat circulating in plasma is bound to proteins. Hydrochlorothiazide is not metabolized. Its apparent volume of distribution is 3.6 to 7.8 L/kg, consistent with measured plasma protein binding of 67.9%. The drug also accumulates in red blood cells, so that whole blood levels are 1.6 to 1.8 times those measured in plasma.
Some placental passage occurred when quinapril was administered to pregnant rats. Studies in rats indicate that quinapril and its metabolites do not cross the blood-brain barrier. Hydrochlorothiazide crosses the placenta freely but not the blood-brain barrier.
Quinaprilat is eliminated primarily by renal excretion, up to 96% of an IV dose, and has an elimination half-life in plasma of approximately 2 hours and a prolonged terminal phase with a half-life of 25 hours. Hydrochlorothiazide is excreted unchanged by the kidney. When plasma levels have been followed for at least 24 hours, the plasma half-life has been observed to vary between 4 to 15 hours. At least 61% of the oral dose is eliminated unchanged within 24 hours.
In patients with renal insufficiency, the elimination half-life of quinaprilat increases as creatinine clearance decreases. There is a linear correlation between plasma quinaprilat clearance and creatinine clearance. In patients with end-stage renal disease, chronic hemodialysis or continuous ambulatory peritoneal dialysis have little effect on the elimination of quinapril and quinaprilat. Elimination of quinaprilat is reduced in elderly patients (≥65 years) and in those with heart failure; this reduction is attributable to decrease in renal function (see DOSAGE AND ADMINISTRATION). Quinaprilat concentrations are reduced in patients with alcoholic cirrhosis due to impaired deesterification of quinapril. In a study of patients with impaired renal function (mean creatinine clearance of 19 mL/min), the half-life of hydrochlorothiazide elimination was lengthened to 21 hours.
The pharmacokinetics of quinapril and quinaprilat are linear over a single-dose range of 5 to 80 mg doses and 40 to 160 mg in multiple daily doses.
Pharmacodynamics and Clinical Effects
Single doses of 20 mg of quinapril provide over 80% inhibition of plasma ACE for 24 hours. Inhibition of the pressor response to angiotensin I is shorter-lived, with a 20 mg dose giving 75% inhibition for about 4 hours, 50% inhibition for about 8 hours, and 20% inhibition at 24 hours. With chronic dosing, however, there is substantial inhibition of angiotensin II levels at 24 hours by doses of 20 to 80 mg.
Administration of 10 to 80 mg of quinapril to patients with mild to severe hypertension results in a reduction of sitting and standing blood pressure to about the same extent with minimal effect on heart rate. Symptomatic postural hypotension is infrequent, although it can occur in patients who are salt- and/or volume-depleted (see WARNINGS).
Antihypertensive activity commences within 1 hour with peak effects usually achieved by 2 to 4 hours after dosing. During chronic therapy, most of the blood pressure lowering effect of a given dose is obtained in 1 to 2 weeks. In multiple-dose studies, 10 to 80 mg per day in single or divided doses lowered systolic and diastolic blood pressure throughout the dosing interval, with a trough effect of about 5 to 11/3 to 7 mm Hg. The trough effect represents about 50% of the peak effect.
While the dose-response relationship is relatively flat, doses of 40 to 80 mg were somewhat more effective at trough than 10 to 20 mg, and twice-daily dosing tended to give a somewhat lower trough blood pressure than once-daily dosing with the same total dose. The antihypertensive effect of quinapril continues during long-term therapy, with no evidence of loss of effectiveness.
Hemodynamic assessments in patients with hypertension indicate that blood pressure reduction produced by quinapril is accompanied by a reduction in total peripheral resistance and renal vascular resistance with little or no change in heart rate, cardiac index, renal blood flow, glomerular filtration rate, or filtration fraction.
Therapeutic effects of quinapril appear to be the same for elderly (≥65 years of age) and younger adult patients given the same daily dosages, with no increase in adverse events in elderly patients. In patients with hypertension, quinapril 10 to 40 mg was similar in effectiveness to captopril, enalapril, propranolol, and thiazide diuretics.
After oral administration of hydrochlorothiazide, diuresis begins within 2 hours, peaks in about 4 hours, and lasts about 6 to 12 hours. Use of quinapril with a thiazide diuretic gives blood pressure lowering effect greater than that seen with either agent alone. In clinical trials of quinapril/hydrochlorothiazide using quinapril doses of 2.5 to 40 mg and hydrochlorothiazide doses of 6.25 to 25 mg, the antihypertensive effects were sustained for at least 24 hours, and increased with increasing dose of either component. Although quinapril monotherapy is somewhat less effective in blacks than in non-blacks, the efficacy of combination therapy appears to be independent of race. By blocking the renin-angiotensin-aldosterone axis, administration of quinapril tends to reduce the potassium loss associated with the diuretic. In clinical trials of quinapril and hydrochlorothiazide, the average change in serum potassium was near zero when 2.5 to 40 mg of quinapril was combined with hydrochlorothiazide 6.25 mg, and the average subject who received 10 to 20/12.5 to 25 mg experienced a milder reduction in serum potassium than that experienced by the average subject receiving the same dose of hydrochlorothiazide monotherapy.

INDICATIONS AND USAGE

Hypertension
Quinapril and hydrochlorothiazide tablets are indicated for the treatment of hypertension, to lower blood pressure. Lowering blood pressure reduces the risk of fatal and nonfatal cardiovascular events, primarily strokes and myocardial infarctions. These benefits have been seen in controlled trials of antihypertensive drugs from a wide variety of pharmacologic classes including the class to which this drug principally belongs. There are no controlled trials demonstrating risk reduction with quinapril and hydrochlorothiazide tablets.
Control of high blood pressure should be part of comprehensive cardiovascular risk management, including, as appropriate, lipid control, diabetes management, antithrombotic therapy, smoking cessation, exercise, and limited sodium intake. Many patients will require more than one drug to achieve blood pressure goals. For specific advice on goals and management, see published guidelines, such as those of the National High Blood Pressure Education Program’s Joint National Committee on Prevention, Detection, Evaluation, and Treatment of High Blood Pressure (JNC).
Numerous antihypertensive drugs, from a variety of pharmacologic classes and with different mechanisms of action, have been shown in randomized controlled trials to reduce cardiovascular morbidity and mortality, and it can be concluded that it is blood pressure reduction, and not some other pharmacologic property of the drugs, that is largely responsible for those benefits. The largest and most consistent cardiovascular outcome benefit has been a reduction in the risk of stroke, but reductions in myocardial infarction and cardiovascular mortality also have been seen regularly.
Elevated systolic or diastolic pressure causes increased cardiovascular risk, and the absolute risk increase per mmHg is greater at higher blood pressures, so that even modest reductions of severe hypertension can provide substantial benefit. Relative risk reduction from blood pressure reduction is similar across populations with varying absolute risk, so the absolute benefit is greater in patients who are at higher risk independent of their hypertension (for example, patients with diabetes or hyperlipidemia), and such patients would be expected to benefit from more aggressive treatment to a lower blood pressure goal.
Some antihypertensive drugs have smaller blood pressure effects (as monotherapy) in black patients, and many antihypertensive drugs have additional approved indications and effects (e.g., on angina, heart failure, or diabetic kidney disease). These considerations may guide selection of therapy.
This fixed combination is not indicated for the initial therapy of hypertension (see DOSAGE AND ADMINISTRATION).
In using quinapril and hydrochlorothiazide tablets, consideration should be given to the fact that another angiotensin-converting enzyme inhibitor, captopril, has caused agranulocytosis, particularly in patients with renal impairment or collagen-vascular disease. Available data are insufficient to show that quinapril does not have a similar risk (see WARNINGS: Neutropenia/Agranulocytosis).
Angioedema in Black Patients
Black patients receiving ACE inhibitor monotherapy have been reported to have a higher incidence of angioedema compared to non-blacks. It should also be noted that in controlled clinical trials, ACE inhibitors have an effect on blood pressure that is less in black patients than in non-blacks.

CONTRAINDICATIONS

Quinapril and hydrochlorothiazide tablets are contraindicated in patients who are hypersensitive to quinapril or hydrochlorothiazide and in patients with a history of angioedema related to previous treatment with an ACE inhibitor.
Quinapril and hydrochlorothiazide tablets are contraindicated in combination with a neprilysin inhibitor (e.g., sacubitril). Do not administer quinapril and hydrochlorothiazide tablets within 36 hours of switching to or from sacubitril/valsartan, a neprilysin inhibitor (see WARNINGS and PRECAUTIONS).
Because of the hydrochlorothiazide components, this product is contraindicated in patients with anuria or hypersensitivity to other sulfonamide-derived drugs.
Do not co-administer quinapril and hydrochlorothiazide tablets with aliskiren:

- in patients with diabetes.

WARNINGS

Anaphylactoid and Possibly Related Reactions
Presumably because angiotensin converting inhibitors affect the metabolism of eicosanoids and polypeptides, including endogenous bradykinin, patients receiving ACE inhibitors (including quinapril) may be subject to a variety of adverse reactions, some of them serious.
Head and Neck Angioedema
Angioedema of the face, extremities, lips, tongue, glottis, and larynx has been reported in patients treated with ACE inhibitors and has been seen in 0.1% of patients receiving quinapril. In two similarly sized US postmarketing quinapril trials that, combined, enrolled over 3,000 black patients and over 19,000 non-blacks, angioedema was reported in 0.3% and 0.55% of blacks (in Study 1 and 2, respectively) and 0.39% and 0.17% of non-blacks. Angioedema associated with laryngeal edema can be fatal. If laryngeal stridor or angioedema of the face, tongue, or glottis occurs, treatment with quinapril and hydrochlorothiazide should be discontinued immediately, the patient treated in accordance with accepted medical care, and carefully observed until the swelling disappears. In instances where swelling is confined to the face and lips, the condition generally resolves without treatment; antihistamines may be useful in relieving symptoms. Where there is involvement of the tongue, glottis, or larynx likely to cause airway obstruction, emergency therapy including, but not limited to, subcutaneous epinephrine solution 1:1000 (0.3 to 0.5 mL) should be promptly administered (see PRECAUTIONS and ADVERSE REACTIONS).
Patients taking concomitant mammalian target of rapamycin (mTOR inhibitor) (e.g., temsirolimus) therapy or a neprilysin inhibitor may be at increased risk for angioedema.
Intestinal Angioedema
Intestinal angioedema has been reported in patients treated with ACE inhibitors. These patients presented with abdominal pain (with or without nausea or vomiting); in some cases there was no prior history of facial angioedema and C-1 esterase levels were normal. The angioedema was diagnosed by procedures including abdominal CT scan or ultrasound, or at surgery, and symptoms resolved after stopping the ACE inhibitor. Intestinal angioedema should be included in the differential diagnosis of patients on ACE inhibitors presenting with abdominal pain.
Patients With a History of Angioedema
Patients with a history of angioedema unrelated to ACE inhibitor therapy may be at increased risk of angioedema while receiving an ACE inhibitor (see also CONTRAINDICATIONS).
Anaphylactoid Reactions During Desensitization
Two patients undergoing desensitizing treatment with Hymenoptera venom while receiving ACE inhibitors sustained life-threatening anaphylactoid reactions. In the same patients, these reactions were avoided when ACE inhibitors were temporarily withheld, but they reappeared upon inadvertent challenge.
Anaphylactoid Reactions During Membrane Exposure
Anaphylactoid reactions have been reported in patients dialyzed with high-flux membranes and treated concomitantly with an ACE inhibitor. Anaphylactoid reactions have also been reported in patients undergoing low-density lipoprotein apheresis with dextran sulfate absorption.
Hepatic Failure
Rarely, ACE inhibitors have been associated with a syndrome that starts with cholestatic jaundice and progresses to fulminant hepatic necrosis and (sometimes) death. The mechanism of this syndrome is not understood. Patients receiving ACE inhibitors who develop jaundice or marked elevations of hepatic enzymes should discontinue the ACE inhibitor and receive appropriate medical follow-up.
Hypotension
Quinapril and hydrochlorothiazide can cause symptomatic hypotension, probably not more frequently than either monotherapy. It was reported in 1.2% of 1,571 patients receiving quinapril and hydrochlorothiazide during clinical trials. Like other ACE inhibitors, quinapril has been only rarely associated with hypotension in uncomplicated hypertensive patients.
Symptomatic hypotension sometimes associated with oliguria and/or progressive azotemia, and rarely acute renal failure and/or death, include patients with the following conditions or characteristics: heart failure, hyponatremia, high dose diuretic therapy, recent intensive diuresis or increase in diuretic dose, renal dialysis or severe volume and/or salt depletion of any etiology. Volume and/or salt depletion should be corrected before initiating therapy with quinapril and hydrochlorothiazide.
Quinapril and hydrochlorothiazide should be used cautiously in patients receiving concomitant therapy with other antihypertensives. The thiazide component of quinapril and hydrochlorothiazide may potentiate the action of other antihypertensive drugs, especially ganglionic or peripheral adrenergic-blocking drugs. The antihypertensive effects of the thiazide component may also be enhanced in the postsympathectomy patients.
In patients at risk of excessive hypotension, therapy with quinapril and hydrochlorothiazide should be started under close medical supervision. Such patients should be followed closely for the first 2 weeks of treatment and whenever the dosage of quinapril or diuretic is increased. Similar considerations may apply to patients with ischemic heart or cerebrovascular disease in whom an excessive fall in blood pressure could result in myocardial infarction or cerebrovascular accident.
If excessive hypotension occurs, the patient should be placed in a supine position and, if necessary, treated with intravenous infusion of normal saline. Quinapril and hydrochlorothiazide treatment usually can be continued following restoration of blood pressure and volume. If symptomatic hypotension develops, a dose reduction or discontinuation of quinapril and hydrochlorothiazide may be necessary.
Impaired Renal Function
Quinapril and hydrochlorothiazide should be used with caution in patients with severe renal disease. Thiazides may precipitate azotemia in such patients, and the effects of repeated dosing may be cumulative.
When the renin-angiotensin-aldosterone system is inhibited by quinapril, changes in renal function may be anticipated in susceptible individuals. In patients with severe congestive heart failure, whose renal function may depend on the activity of the renin-angiotensin-aldosterone system, treatment with angiotensin-converting enzyme inhibitors (including quinapril) may be associated with oliguria and/or progressive azotemia and (rarely) with acute renal failure and/or death.
In clinical studies in hypertensive patients with unilateral renal artery stenosis, treatment with ACE inhibitors was associated with increases in blood urea nitrogen and serum creatinine; these increases were reversible upon discontinuation of ACE inhibitor, concomitant diuretic, or both. When such patients are treated with quinapril and hydrochlorothiazide, renal function should be monitored during the first few weeks of therapy.
Some quinapril-treated hypertensive patients with no apparent preexisting renal vascular diseases have developed increases in blood urea nitrogen and serum creatinine, usually minor and transient, especially when quinapril has been given concomitantly with a diuretic. This is more likely to occur in patients with pre-existing renal impairment. Dosage reduction of quinapril and hydrochlorothiazide may be required. Evaluation of the hypertensive patients should also include assessment of the renal function (see DOSAGE AND ADMINISTRATION).

Neutropenia/Agranulocytosis

Another ACE inhibitor, captopril, has been shown to cause agranulocytosis and bone marrow depression rarely in patients with uncomplicated hypertension, but more frequently in patients with renal impairment, especially if they also have a collagen vascular disease, such as systemic lupus erythematosus or scleroderma. Agranulocytosis did occur during quinapril treatment in one patient with a history of neutropenia during previous captopril therapy. Available data from clinical trials of quinapril are insufficient to show that, in patients without prior reactions to other ACE inhibitors, quinapril does not cause agranulocytosis at similar rates. As with other ACE inhibitors, periodic monitoring of white blood cell counts in patients with collagen vascular disease and/or renal disease should be considered.

Fetal Toxicity

Use of drugs that act on the renin-angiotensin system during the second and third trimesters of pregnancy reduces fetal renal function and increases fetal and neonatal morbidity and death. Resulting oligohydramnios can be associated with fetal lung hypoplasia and skeletal deformations. Potential neonatal adverse effects include skull hypoplasia, anuria, hypotension, renal failure, and death. When pregnancy is detected, discontinue quinapril and hydrochlorothiazide as soon as possible. These adverse outcomes are usually associated with use of these drugs in the second and third trimester of pregnancy. Most epidemiologic studies examining fetal abnormalities after exposure to antihypertensive use in the first trimester have not distinguished drugs affecting the renin-angiotensin system from other antihypertensive agents. Appropriate management of maternal hypertension during pregnancy is important to optimize outcomes for both mother and fetus.
In the unusual case that there is no appropriate alternative to therapy with drugs affecting the renin-angiotensin system for a particular patient, apprise the mother of the potential risk to the fetus. Perform serial ultrasound examinations to assess the intra-amniotic environment. If oligohydramnios is observed, discontinue quinapril and hydrochlorothiazide, unless it is considered life-saving for the mother. Fetal testing may be appropriate, based on the week of pregnancy. Patients and physicians should be aware, however, that oligohydramnios may not appear until after the fetus has sustained irreversible injury. Closely observe infants with histories of in utero exposure to quinapril and hydrochlorothiazide for hypotension, oliguria, and hyperkalemia (see PRECAUTIONS, Pediatric Use).
Intrauterine exposure to thiazide diuretics is associated with fetal or neonatal jaundice, thrombocytopenia, and possibly other adverse reactions that occurred in adults.
No teratogenic effects of quinapril were seen in studies of pregnant rats and rabbits. On a mg/kg basis, the doses used were up to 180 times (in rats) and one time (in rabbits) the maximum recommended human dose. No teratogenic effects of quinapril and hydrochlorothiazide were seen in studies of pregnant rats and rabbits. On a mg/kg (quinapril/hydrochlorothiazide) basis, the doses used were up to 188/94 times (in rats) and 0.6/0.3 times (in rabbits) the maximum recommended human dose.
Impaired Hepatic Function
Quinapril and hydrochlorothiazide should be used with caution in patients with impaired hepatic function or progressive liver disease, since minor alterations of fluid and electrolyte balance may precipitate hepatic coma. Also, since the metabolism of quinapril to quinaprilat is normally dependent upon hepatic esterases, patients with impaired liver function could develop markedly elevated plasma levels of quinapril. No normal pharmacokinetic studies have been carried out in hypertensive patients with impaired liver function.
Systemic Lupus Erythematosus
Thiazide diuretics have been reported to cause exacerbation or activation of systemic lupus erythematosus.
Acute Angle-Closure Glaucoma with or without Acute Myopia and Choroidal
Effusions: Hydrochlorothiazide, a sulfonamide, can cause an idiosyncratic reaction, resulting in acute angle-closure glaucoma and elevated intraocular pressure with or without a noticeable acute myopic shift and/or choroidal effusions. Symptoms may include acute onset of decreased visual acuity or ocular pain and typically occur within hours to weeks of drug initiation. Untreated, the angle-closure glaucoma may result in permanent visual field loss. The primary treatment is to discontinue hydrochlorothiazide as rapidly as possible. Prompt medical or surgical treatments may need to be considered if the intraocular pressure remains uncontrolled. Risk factors for developing acute angle-closure glaucoma may include a history of sulfonamide or penicillin allergy.

PRECAUTIONS

General

Serum Electrolyte Abnormalities
In clinical trials, hyperkalemia (serum potassium ≥5.8 mmol/L) occurred in approximately 2% of patients receiving quinapril. In most cases, elevated serum potassium levels were isolated values which resolved despite continued therapy. Less than 0.1% of patients discontinued therapy due to hyperkalemia. Risk factors for the development of hyperkalemia include renal insufficiency, diabetes mellitus, and the concomitant use of other drugs that raise serum potassium levels.
Hydrochlorothiazide can cause hypokalemia and hyponatremia. Hypomagnesemia can result in hypokalemia which appears difficult to treat despite potassium repletion. Drugs that inhibit the renin-angiotensin system can cause hyperkalemia. The risk of hyperkalemia may be increased in patients with renal insufficiency, diabetes mellitus or with concomitant use of drugs that raise serum potassium (see DRUG INTERACTIONS). The risk of hypokalemia may be increased in patients with cirrhosis, brisk diuresis, or with concomitant use of drugs that lower serum potassium. Monitor serum electrolytes periodically.
Other Metabolic Disturbances
Hydrochlorothiazide may alter glucose tolerance and raise serum levels of cholesterol and triglycerides.
Hydrochlorothiazide may raise the serum uric acid level due to reduced clearance of uric acid and may cause or exacerbate hyperuricemia and precipitate gout in susceptible patients.
Hydrochlorothiazide decreases urinary calcium excretion and may cause elevations of serum calcium. Monitor calcium levels in patients with hypercalcemia receiving quinapril and hydrochlorothiazide.
Cough
Presumably due to the inhibition of the degradation of endogenous bradykinin, persistent nonproductive cough has been reported with all ACE inhibitors, resolving after discontinuation of therapy. ACE inhibitor-induced cough should be considered in the differential diagnosis of cough.
Surgery/Anesthesia
In patients undergoing surgery or during anesthesia with agents that produce hypotension, quinapril will block the angiotensin II formation that could otherwise occur secondary to compensatory renin release. Hypotension that occurs as a result of this mechanism can be corrected by volume expansion.

Information for Patients

Angioedema
Angioedema, including laryngeal edema, can occur with treatment with ACE inhibitors, especially following the first dose. Tell patients receiving quinapril and hydrochlorothiazide to immediately report any signs or symptoms suggesting angioedema (swelling of face, eyes, lips, or tongue, or difficulty in breathing) and to temporarily discontinue quinapril and hydrochlorothiazide until after consulting with the prescribing physician.
Pregnancy
Tell female patients of childbearing age about the consequences of exposure to quinapril and hydrochlorothiazide during pregnancy. Discuss treatment options with women planning to become pregnant. Ask patients to report pregnancies to their physicians as soon as possible.
Symptomatic Hypotension
Tell patients receiving quinapril and hydrochlorothiazide that lightheadedness can occur, especially during the first days of therapy, and to report it to the prescribing physician. Tell the patient if syncope occurs, discontinue quinapril and hydrochlorothiazide until the physician has been consulted.
Tell patients that inadequate fluid intake, excessive perspiration, diarrhea, or vomiting can lead to an excessive fall in blood pressure because of reduction in fluid volume, with the same consequences of lightheadedness and possible syncope.
Tell patients planning to undergo major surgery and/ or general or spinal anesthesia to inform their physicians that they are taking an ACE inhibitor.
Hyperkalemia
Tell patients receiving quinapril and hydrochlorothiazide not to use potassium supplements or salt substitutes containing potassium without consulting the prescribing physician.
Neutropenia
Tell patients to promptly report any indication of infection (e.g., sore throat, fever) which could be a sign of neutropenia.
Non-melanoma Skin Cancer: Instruct patients taking hydrochlorothiazide to protect skin from the sun and undergo regular skin cancer screening.
NOTE: As with many other drugs, certain advice to patients being treated with quinapril is warranted. This information is intended to aid in the safe and effective use of this medication. It is not a disclosure of all possible adverse or intended effects.

Laboratory Tests

The hydrochlorothiazide component of quinapril and hydrochlorothiazide may decrease serum PBI levels without signs of thyroid disturbance.
Therapy with quinapril and hydrochlorothiazide should be interrupted for a few days before carrying out tests of parathyroid function.

Drug Interactions

Agents Increasing Serum Potassium
Coadministration of quinapril and hydrochlorothiazide with other drugs that raise serum potassium levels may result in hyperkalemia. Monitor serum potassium in such patients.
Lithium
Increased serum lithium levels and symptoms of lithium toxicity have been reported in patients receiving ACE inhibitors during therapy with lithium. Because renal clearance of lithium is reduced by thiazides, the risk of lithium toxicity is presumably raised further when, as in therapy with quinapril and hydrochlorothiazide, a thiazide diuretic is coadministered with the ACE inhibitor. Quinapril and hydrochlorothiazide and lithium should be coadministered with caution, and frequent monitoring of serum lithium levels is recommended.
Dual Blockade of the Renin-Angiotensin System (RAS)
Dual blockade of the RAS with angiotensin receptor blockers, ACE inhibitors, or aliskiren is associated with increased risks of hypotension, hyperkalemia, and changes in renal function (including acute renal failure) compared to monotherapy. Most patients receiving the combination of two RAS inhibitors do not obtain any additional benefit compared to monotherapy. In general, avoid combined use of RAS inhibitors. Closely monitor blood pressure, renal function and electrolytes in patients on quinapril and hydrochlorothiazide and other agents that affect the RAS.
Do not co-administer aliskiren with quinapril and hydrochlorothiazide in patients with diabetes. Avoid concomitant use of aliskiren with quinapril and hydrochlorothiazide in patients with renal impairment (GFR <60 mL/min/1.73 m^2).
Tetracycline and Other Drugs That Interact with Magnesium
Simultaneous administration of tetracycline with quinapril reduced the absorption of tetracycline by approximately 28% to 37%, possibly due to the high magnesium content in quinapril tablets. This interaction should be considered if coprescribing quinapril and tetracycline or other drugs that interact with magnesium.
Gold
Nitritoid reactions (symptoms include facial flushing, nausea, vomiting, and hypotension) have been reported rarely in patients on therapy with injectable gold (sodium aurothiomalate) and concomitant ACE inhibitor therapy.
Non-Steroidal Anti-Inflammatory Agents including Selective Cyclooxygenase-2 Inhibitors (COX-2 Inhibitors)
In patients who are elderly, volume-depleted (including those on diuretic therapy), or with compromised renal function, co-administration of NSAIDs, including selective COX-2 inhibitors, with ACE inhibitors, including quinapril, may result in deterioration of renal function, including possible acute renal failure. These effects are usually reversible. Monitor renal function periodically in patients receiving quinapril and NSAID therapy.
The antihypertensive effect of ACE inhibitors, including quinapril may be attenuated by NSAIDs.
Agents that Inhibit mTOR or Other Drugs Known to Cause Angioedema: Patients taking concomitant mTOR inhibitor (e.g., temsirolimus) therapy or a neprilysin inhibitor may be at increased risk for angioedema.
Other Agents
Drug interaction studies of quinapril and other agents showed:

- Multiple dose therapy with propranolol or cimetidine has no effect on the pharmacokinetics of single doses of quinapril.
- The anticoagulant effect of a single dose of warfarin (measured by prothrombin time) was not significantly changed by quinapril coadministration twice daily.
- Digoxin: Thiazide-induced electrolyte disturbances, i.e. hypokalemia, hypomagnesemia, increase the risk of digoxin toxicity, which may lead to fatal arrhythmic events (See PRECAUTIONS).
- No pharmacokinetic interaction was observed when single doses of quinapril and hydrochlorothiazide were administered concomitantly.

When administered concurrently, the following drugs may interact with thiazide diuretics.

- Alcohol, Barbiturates, or Narcotics—potentiation of orthostatic hypotension may occur.
- Antidiabetic Drugs (oral hypoglycemic agents and insulin)—dosage adjustments of the antidiabetic drug may be required (See PRECAUTIONS).
- Cholestyramine and Colestipol Resin—absorption of hydrochlorothiazide is impaired in the presence of anionic exchange resins. Single doses of either cholestyramine or colestipol resins bind the hydrochlorothiazide and reduce its absorption from the gastrointestinal tract by up to 85% and 43%, respectively.
- Corticosteroids, ACTH—intensified electrolyte depletion, particularly hypokalemia.
- Pressor Amines (e.g., norepinephrine)—possible decreased response to pressor amines, but not sufficient to preclude their therapeutic use.
- Skeletal Muscle Relaxants, Nondepolarizing (e.g., tubocurarine)—possible increased responsiveness to the muscle relaxant.
- Non-steroidal Anti-inflammatory Drugs—the diuretic, natriuretic, and antihypertensive effects of thiazide diuretics may be reduced by concurrent administration of nonsteroidal anti-inflammatory agents.

Carcinogenesis, Mutagenesis, Impairment of Fertility

Carcinogenicity, mutagenicity, and fertility studies have not been conducted in animals with quinapril and hydrochlorothiazide.
Quinapril hydrochloride was not carcinogenic in mice or rats when given in doses up to 75 or 100 mg/kg/day (50 or 60 times the maximum human daily dose, respectively, on a mg/kg basis and 3.8 or 10 times the maximum human daily dose on a mg/m^2 basis) for 104 weeks. Female rats given the highest dose level had an increased incidence of mesenteric lymph node hemangiomas and skin/subcutaneous lipomas. Neither quinapril nor quinaprilat were mutagenic in the Ames bacterial assay with or without metabolic activation. Quinapril was also negative in the following genetic toxicology studies: in vitro mammalian cell point mutation, sister chromatid exchange in cultured mammalian cells, micronucleus test with mice, in vitro chromosome aberration with V79 cultured lung cells, and in an in vivo cytogenetic study with rat bone marrow. There were no adverse effects on fertility or reproduction in rats at doses up to 100 mg/kg/day (60 and 10 times the maximum daily human dose when based on mg/kg and mg/m^2, respectively).
Under the auspices of the National Toxicology Program, rats and mice received hydrochlorothiazide in their feed for 2 years, at doses up to 600 mg/kg/day in mice and up to 100 mg/kg/day in rats. These studies uncovered no evidence of a carcinogenic potential of hydrochlorothiazide in rats or female mice, but there was “equivocal” evidence of hepatocarcinogenicity in male mice. Hydrochlorothiazide was not genotoxic in in vitro assays using strains TA 98, TA 100, TA 1535, TA 1537, and TA 1538 of Salmonella typhimurium (the Ames test); in the Chinese hamster ovary (CHO) test for chromosomal aberrations; or in vivo assays using mouse germinal cell chromosomes, Chinese hamster bone marrow chromosomes, and the Drosophila sex-linked recessive lethal trait gene. Positive test results were obtained in the in vitro CHO sister chromatid exchange (clastogenicity) test and in the mouse lymphoma cell (mutagenicity) assays, using concentrations of hydrochlorothiazide of 43 to 1300 mcg/mL. Positive test results were also obtained in the Aspergillus nidulans nondisjunction assay, using an unspecified concentration of hydrochlorothiazide.
Hydrochlorothiazide had no adverse effects on the fertility of mice and rats of either sex in studies wherein these species were exposed, via their diets, to doses of up to 100 and 4 mg/kg/day, respectively, prior to mating and throughout gestation.

Nursing Mothers

Because quinapril and hydrochlorothiazide are secreted in human milk, caution should be exercised when quinapril and hydrochlorothiazide is administered to a nursing woman.
Because of the potential for serious adverse reactions in nursing infants from hydrochlorothiazide and the unknown effects of quinapril in infants, a decision should be made whether to discontinue nursing or to discontinue quinapril and hydrochlorothiazide, taking into account the importance of the drug to the mother.

Geriatric Use

Clinical studies of quinapril hydrochloride/hydrochlorothiazide did not include sufficient numbers of subjects aged 65 and over to determine whether they respond differently from younger subjects. Other reported clinical experience has not identified differences in responses between the elderly and younger patients. In general, dose selection for an elderly patient should be cautious, usually starting at the low end of the dosing range, reflecting the greater frequency of decreased hepatic, renal, or cardiac function, and of concomitant disease or other drug therapy.

Pediatric Use

Neonates with a history of in utero exposure to quinapril and hydrochlorothiazide
If oliguria or hypotension occurs, direct attention toward support of blood pressure and renal perfusion. Exchange transfusions or dialysis may be required as a means of reversing hypotension and/or substituting for disordered renal function. Removal of quinapril, which crosses the placenta, from the neonatal circulation is not significantly accelerated by these means.
Safety and effectiveness of quinapril and hydrochlorothiazide in children have not been established.

ADVERSE REACTIONS

Quinapril and hydrochlorothiazide has been evaluated for safety in 1571 patients in controlled and uncontrolled studies. Of these, 498 were given quinapril plus hydrochlorothiazide for at least 1 year, with 153 patients extending combination therapy for over 2 years. In clinical trials with quinapril and hydrochlorothiazide, no adverse experience specific to the combination has been observed. Adverse experiences that have occurred have been limited to those that have been previously reported with quinapril or hydrochlorothiazide.
Adverse experiences were usually mild and transient, and there was no relationship between side effects and age, sex, race, or duration of therapy. Discontinuation of therapy because of adverse effects was required in 2.1% in patients in controlled studies. The most common reasons for discontinuation of therapy with quinapril and hydrochlorothiazide were cough (1%; see PRECAUTIONS) and headache (0.7%).
Adverse experiences probably or possibly related to therapy or of unknown relationship to therapy occurring in 1% or more of the 943 patients treated with quinapril plus hydrochlorothiazide in controlled trials are shown below.

 | Percent of Patients in Controlled Trials
 | Quinapril/HCTZ N = 943 | Placebo N = 100
Headache | 6.7 | 30
Dizziness | 4.8 | 4
Coughing | 3.2 | 2
Fatigue | 2.9 | 3
Myalgia | 2.4 | 5
Viral Infection | 1.9 | 4
Rhinitis | 2 | 3
Nausea and/or Vomiting | 1.8 | 6
Abdominal Pain | 1.7 | 4
Back Pain | 1.5 | 2
Diarrhea | 1.4 | 1
Upper Respiratory Infection | 1.3 | 4
Insomnia | 1.2 | 2
Somnolence | 1.2 | 0
Bronchitis | 1.2 | 1
Dyspepsia | 1.2 | 2
Asthenia | 1.1 | 1
Pharyngitis | 1.1 | 2
Vasodilatation | 1 | 1
Vertigo | 1 | 2
Chest Pain | 1 | 2

Clinical adverse experiences probably, possibly, or definitely related or of uncertain relationship to therapy occurring in ≥0.5% to <1% (except as noted) of the patients treated with quinapril/HCTZ in controlled and uncontrolled trials (N=1571) and less frequent, clinically significant events seen in clinical trials or postmarketing experience (the rarer events are in italics) include (listed by body system):

BODY AS A WHOLE: | Asthenia, Malaise
CARDIOVASCULAR: | Palpitation, Tachycardia, Heart Failure, Hyperkalemia, Myocardial Infarction, Cerebrovascular Accident, Hypertensive Crisis, Angina Pectoris, Orthostatic Hypotension, Cardiac Rhythm Disturbance
GASTROINTESTINAL: | Mouth or Throat Dry, Gastrointestinal Hemorrhage, Pancreatitis, Abnormal Liver Function Tests
NERVOUS/PSYCHIATRIC: | Nervousness, Vertigo, Paresthesia
RESPIRATORY: | Sinusitis, Dyspnea
INTEGUMENTARY: | Pruritus, Sweating Increased, Erythema Multiforme, Exfoliative Dermatitis, Photosensitivity Reaction, Alopecia, Pemphigus
UROGENITAL SYSTEM: OTHER: | Acute Renal Failure, Impotence Agranulocytosis, Thrombocytopenia, Arthralgia
Angioedema: | Angioedema has been reported in 0.1% of patients receiving quinapril (0.1%) (see WARNINGS).

Postmarketing Experience
The following serious nonfatal adverse events, regardless of their relationship to quinapril and HCTZ combination tablets, have been reported during extensive postmarketing experience:
Non-melanoma Skin Cancer: Hydrochlorothiazide is associated with an increased risk of non-melanoma skin cancer. In a study conducted in the Sentinel System, increased risk was predominantly for squamous cell carcinoma (SCC) and in white patients taking large cumulative doses. The increased risk for SCC in the overall population was approximately 1 additional case per 16,000 patients per year, and for white patients taking a cumulative dose of ≥50,000 mg the risk increase was approximately 1 additional SCC case for every 6,700 patients per year.
BODY AS A WHOLE: Shock, accidental injury, neoplasm, cellulitis, ascites, generalized edema, hernia and anaphylactoid reaction.
CARDIOVASCULAR SYSTEM: Bradycardia, cor pulmonale, vasculitis, and deep vein thrombosis.
DIGESTIVE SYSTEM: Gastrointestinal carcinoma, cholestatic jaundice, hepatitis, esophagitis, vomiting, and diarrhea.
EYE DISORDERS: Acute myopia and acute angle closure glaucoma (see WARNINGS).
HEMIC SYSTEM: Anemia.
METABOLIC AND NUTRITIONAL DISORDERS: Weight loss.
MUSCULOSKELETAL SYSTEM: Myopathy, myositis, and arthritis.
NERVOUS SYSTEM: Paralysis, hemiplegia, speech disorder, abnormal gait, meningism, and amnesia.
RESPIRATORY SYSTEM: Pneumonia, asthma, respiratory infiltration, and lung disorder.
SKIN AND APPENDAGES: Urticaria, macropapular rash, and petechiases.
SPECIAL SENSES: Abnormal vision.
UROGENITAL SYSTEM: Kidney function abnormal, albuminuria, pyuria, hematuria, and nephrosis.
Quinapril monotherapy has been evaluated for safety in 4960 patients. In clinical trials adverse events which occurred with quinapril were also seen with quinapril and hydrochlorothiazide. In addition, the following were reported for quinapril at an incidence >0.5%: depression, back pain, constipation, syncope, and amblyopia.
Hydrochlorothiazide has been extensively prescribed for many years, but there has not been enough systematic collection of data to support an estimate of the frequency of the observed adverse reactions. Within organ-system groups, the reported reactions are listed here in decreasing order of severity, without regard to frequency.

BODY AS A WHOLE: | Weakness.
CARDIOVASCULAR: | Orthostatic hypotension (may be potentiated by alcohol, barbiturates, or narcotics).
DIGESTIVE: | Pancreatitis, jaundice (intrahepatic cholestatic), sialadenitis, vomiting, diarrhea, cramping, nausea, gastric irritation, constipation, and anorexia.
NEUROLOGIC: | Vertigo, lightheadedness, transient blurred vision, headache, paresthesia, xanthopsia, weakness, and restlessness.
MUSCULOSKELETAL: | Muscle spasm.
HEMATOLOGIC: | Aplastic anemia, agranulocytosis, leukopenia, thrombocytopenia, and hemolytic anemia.
RENAL: | Renal failure, renal dysfunction, interstitial nephritis (see WARNINGS).
METABOLIC: | Hyperglycemia, glycosuria, and hyperuricemia.
HYPERSENSITIVITY: | Necrotizing angiitis, Stevens-Johnson syndrome, respiratory distress (including pneumonitis and pulmonary edema), purpura, urticaria, rash, and photosensitivity.

Clinical Laboratory Test Findings
Serum Electrolytes: See PRECAUTIONS.
Creatinine, Blood Urea Nitrogen
Increases (>1.25 times the upper limit of normal) in serum creatinine and blood urea nitrogen were observed in 3% and 4%, respectively, of patients treated with quinapril and hydrochlorothiazide. Most increases were minor and reversible, which can occur in patients with essential hypertension but most frequently in patients with renal artery stenosis (see PRECAUTIONS).
PBI and Tests of Parathyroid Function: See PRECAUTIONS.
Hematology: See WARNINGS.
Other (causal relationships unknown)
Other clinically important changes in standard laboratory tests were rarely associated with quinapril and hydrochlorothiazide administration. Elevations in uric acid, glucose, magnesium, cholesterol, triglyceride, and calcium (see PRECAUTIONS) have been reported.

OVERDOSAGE

No specific information is available on the treatment of overdosage with quinapril and hydrochlorothiazide or quinapril monotherapy; treatment should be symptomatic and supportive. Therapy with quinapril and hydrochlorothiazide should be discontinued, and the patient should be observed. Dehydration, electrolyte imbalance, and hypotension should be treated by established procedures.
The oral median lethal dose of quinapril/hydrochlorothiazide in combination ranges from 1063/664 to 4640/2896 mg/kg in mice and rats. Doses of 1440 to 4280 mg/kg of quinapril cause significant lethality in mice and rats. In single-dose studies of hydrochlorothiazide, most rats survived doses up to 2.75 g/kg.
Data from human overdoses of ACE inhibitors are scanty; the most likely manifestation of human quinapril overdosage is hypotension. In human hydrochlorothiazide overdose, the most common signs and symptoms observed have been those of dehydration and electrolyte depletion (hypokalemia, hypochloremia, hyponatremia). If digitalis has also been administered, hypokalemia may accentuate cardiac arrhythmias.
Laboratory determinations of serum levels of quinapril and its metabolites are not widely available, and such determinations have, in any event, no established role in the management of quinapril overdose.
No data are available to suggest physiological maneuvers (e.g., maneuvers to change the pH of the urine) that might accelerate elimination of quinapril and its metabolites. Hemodialysis and peritoneal dialysis have little effect on the elimination of quinapril and quinaprilat.
Angiotensin II could presumably serve as a specific antagonist-antidote in the setting of quinapril overdose, but angiotensin II is essentially unavailable outside of scattered research facilities. Because the hypotensive effect of quinapril is achieved through vasodilation and effective hypovolemia, it is reasonable to treat quinapril overdose by infusion of normal saline solution.

DOSAGE AND ADMINISTRATION

As individual monotherapy, quinapril is an effective treatment of hypertension in once-daily doses of 10 mg to 80 mg and hydrochlorothiazide is effective in doses of 12.5 mg to 50 mg. In clinical trials of quinapril/hydrochlorothiazide combination therapy using quinapril doses of 2.5 mg to 40 mg and hydrochlorothiazide doses of 6.25 mg to 25 mg, the antihypertensive effects increased with increasing dose of either component.
The side effects (see WARNINGS) of quinapril are generally rare and apparently independent of dose; those of hydrochlorothiazide are a mixture of dose-dependent phenomena (primarily hypokalemia) and dose-independent phenomena (e.g., pancreatitis), the former much more common than the latter. Therapy with any combination of quinapril and hydrochlorothiazide will be associated with both sets of dose-independent side effects, but regimens that combine low doses of hydrochlorothiazide with quinapril produce minimal effects on serum potassium. In clinical trials of quinapril and hydrochlorothiazide tablets, the average change in serum potassium was near zero in subjects who received HCTZ 6.25 mg in the combination, and the average subject who received 10 mg to 40 mg/12.5 mg to 25 mg experienced a milder reduction in serum potassium than that experienced by the average subject receiving the same dose of hydrochlorothiazide monotherapy.
To minimize dose-independent side effects, it is usually appropriate to begin combination therapy only after a patient has failed to achieve the desired effect with monotherapy.
Therapy Guided by Clinical Effect
Patients whose blood pressures are not adequately controlled with quinapril monotherapy may instead be given quinapril and hydrochlorothiazide tablets 10 mg/12.5 mg or 20 mg/12.5 mg. Further increases of either or both components could depend on clinical response. The hydrochlorothiazide dose should generally not be increased until 2 to 3 weeks have elapsed. Patients whose blood pressures are adequately controlled with 25 mg of daily hydrochlorothiazide, but who experience significant potassium loss with this regimen, may achieve blood pressure control with less electrolyte disturbance if they are switched to quinapril and hydrochlorothiazide tablets 10 mg/12.5 mg or 20 mg/12.5 mg.
Replacement Therapy
For convenience, patients who are adequately treated with 20 mg of quinapril and 25 mg of hydrochlorothiazide and experience no significant electrolyte disturbances may instead wish to receive quinapril and hydrochlorothiazide tablets 20 mg/25 mg.
Use in Renal Impairment
Regimens of therapy with quinapril and hydrochlorothiazide tablets need not take account of renal function as long as the patient’s creatinine clearance is >30 mL/min/1.73 m^2 (serum creatinine roughly ≤3 mg/dL or 265 µmol/L). In patients with more severe renal impairment, loop diuretics are preferred to thiazides. Therefore, quinapril and hydrochlorothiazide tablets are not recommended for use in these patients.

HOW SUPPLIED

Quinapril and Hydrochlorothiazide Tablets, USP 10 mg/12.5 mg are Pink colored, scored, oval shaped, biconvex, film-coated tablets debossed with ‘D’ on scored side and ‘18’ on other side.

Bottles of 90 NDC 65862-161-90

Quinapril and Hydrochlorothiazide Tablets, USP 20 mg/12.5 mg are Pink colored, scored, round shaped, biconvex, film-coated tablets debossed with ‘D’ on scored side and ‘19’ on other side.

Bottles of 30 NDC 65862-162-30
Bottles of 90 NDC 65862-162-90

Quinapril and Hydrochlorothiazide Tablets, USP 20 mg/25 mg are Pink colored, round shaped, biconvex, film-coated tablets debossed with ‘D’ on one side and ‘20’ on other side.

Bottles of 90 NDC 65862-163-90

Store at 20° to 25°C (68° to 77°F); excursions permitted to 15° to 30°C (59° to 86°F) [see USP Controlled Room Temperature]. Protect from light.

Distributed by:
Aurobindo Pharma USA, Inc.
279 Princeton-Hightstown Road
East Windsor, NJ 08520
Manufactured by:
Aurobindo Pharma Limited
Hyderabad–500 032, India
Revised: 05/2022

PACKAGE LABEL-PRINCIPAL DISPLAY PANEL - 10 mg/12.5 mg (90 Tablet Bottle)

NDC 65862-161-90
Rx only
Quinapril and
Hydrochlorothiazide
Tablets, USP
10 mg/12.5 mg
AUROBINDO 90 Tablets

PACKAGE LABEL-PRINCIPAL DISPLAY PANEL - 20 mg/12.5 mg (90 Tablet Bottle)

NDC 65862-162-90
Rx only
Quinapril and
Hydrochlorothiazide
Tablets, USP
20 mg/12.5 mg
AUROBINDO 90 Tablets

PACKAGE LABEL-PRINCIPAL DISPLAY PANEL - 20 mg/25 mg (90 Tablet Bottle)

NDC 65862-163-90
Rx only
Quinapril and
Hydrochlorothiazide
Tablets, USP
20 mg/25 mg
AUROBINDO 90 Tablets